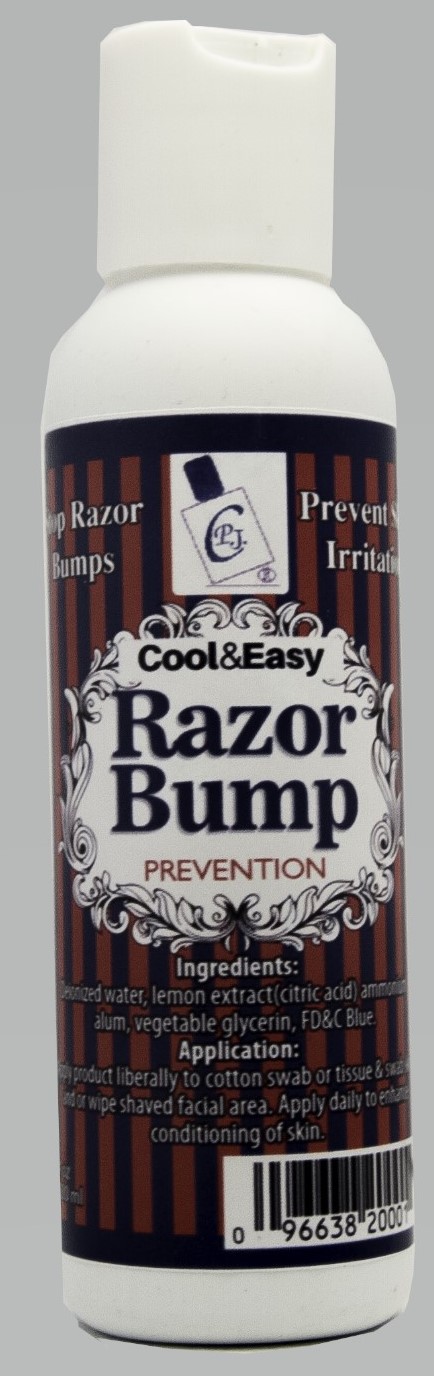 DRUG LABEL: Cool and Easy Razor Bump Prevention
NDC: 72486-101 | Form: SOLUTION
Manufacturer: Casanova P. Jackson
Category: otc | Type: HUMAN OTC DRUG LABEL
Date: 20180628

ACTIVE INGREDIENTS: WITCH HAZEL 1 g/1 mL
INACTIVE INGREDIENTS: GLYCERIN; AMMONIUM ALUM ANHYDROUS; ANHYDROUS CITRIC ACID; WATER

ACTIVE INGREDIENT

Witch Hazel

INACTIVE INGREDIENT

aluminum alum, citric acid, deionized water , vegetable glycerin.

INDICATIONS AND USAGE

Cool & Easy Razor Bump Prevention stops razor bumps and prevent skin irritation from shaving.

PURPOSE

The purpose of the Cool & Easy is to stop razor bumps pseudofolliculitis barbae from shaving. It also stops skin irritation and bleeding of the skin from shaving.

DOSAGE AND ADMINISTRATION

The amount used is approximately 2 ml applied tto skin with a cotton swab or cotton applicator. This should be repeated until the entire shaving area has be covered.

Keep out of reach of children because Cool & Easy is to be used topically only.

WARNINGS

Product is to be used externally only.